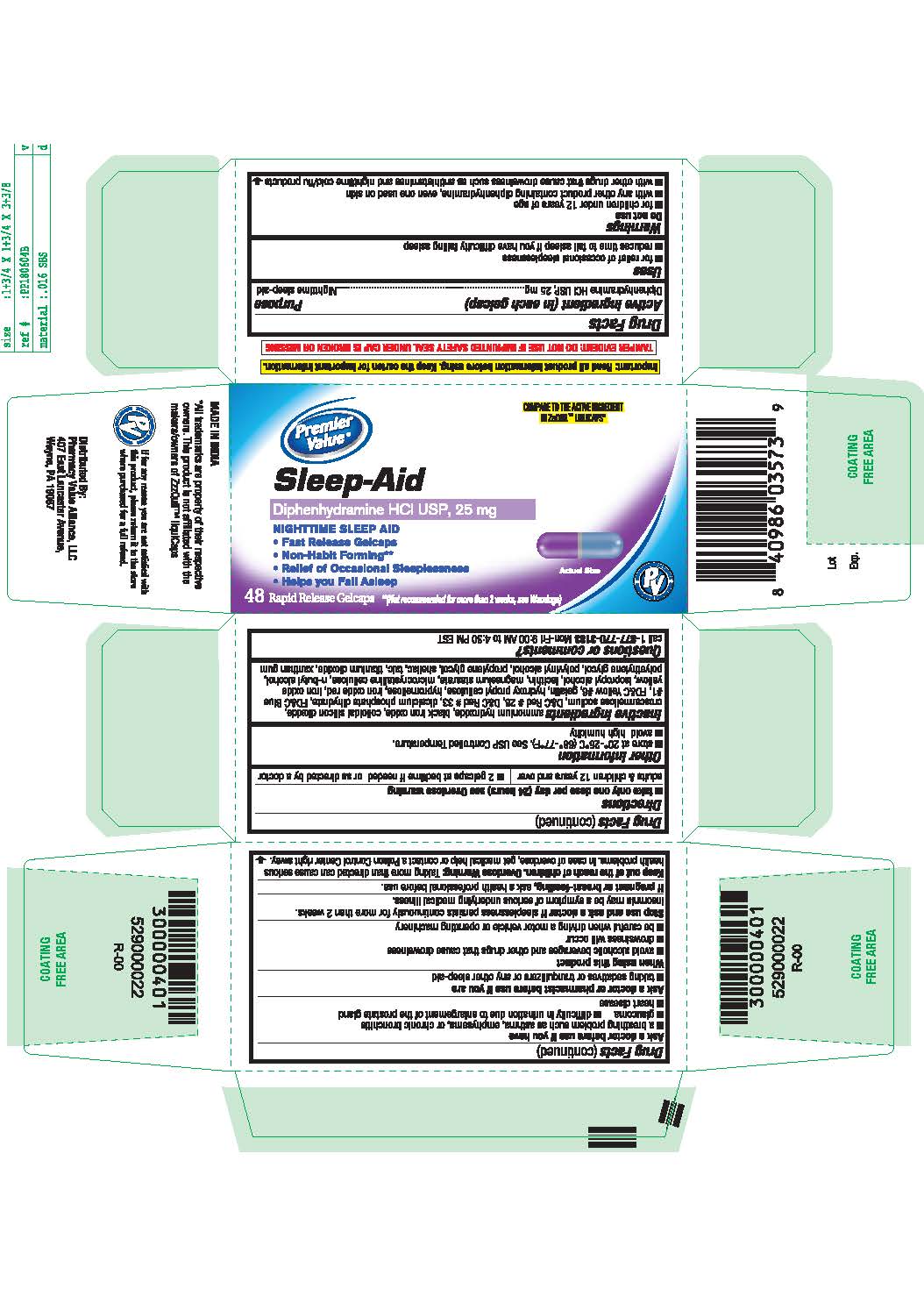 DRUG LABEL: Diphenhydramine Hydrochloride
NDC: 68016-795 | Form: TABLET
Manufacturer: PHARMACY VALUE ALLIANCE, LLC
Category: otc | Type: HUMAN OTC DRUG LABEL
Date: 20210129

ACTIVE INGREDIENTS: DIPHENHYDRAMINE HYDROCHLORIDE 50 mg/1 1
INACTIVE INGREDIENTS: MICROCRYSTALLINE CELLULOSE; TITANIUM DIOXIDE; ANHYDROUS DIBASIC CALCIUM PHOSPHATE; PROPYLENE GLYCOL; TALC; AMMONIA; XANTHAN GUM; ISOPROPYL ALCOHOL; FERROSOFERRIC OXIDE; FD&C BLUE NO. 1; FD&C YELLOW NO. 6; D&C RED NO. 33; BUTYL ALCOHOL; SHELLAC; SILICON DIOXIDE; GELATIN; HYDROXYPROPYL CELLULOSE, UNSPECIFIED; HYPROMELLOSE, UNSPECIFIED; MAGNESIUM STEARATE; POLYVINYL ALCOHOL, UNSPECIFIED; CROSCARMELLOSE SODIUM; LECITHIN, SOYBEAN; POLYETHYLENE GLYCOL, UNSPECIFIED

Nighttime Sleep-Aid
Diphenhydramine HCl USP, 50 mg
NIGHTTIME SLEEP-AID
Rapid Release

Active ingredient

(in each gelcap)

Diphenhydramine HCl USP 50 mg

Purpose

Nighttime sleep-aid

Uses

■ for relief of occasional sleeplessness

Do Not Use

■ for children under 12 years of age

■ with any other product containing diphenhydramine, even one used on skin

Ask a doctor before use if you have

■ a breathing problem such as emphysema, or chronic bronchitis

■ glaucoma

■ difficulty in urination due to enlargement of the prostate gland

Ask a doctor or pharmacist before use if you are

taking sedatives or tranquilizers

When using this product

■ avoid alcoholic beverages

Stop use and ask a doctor if

sleeplessness persists continuously for more than 2 weeks. Insomnia may be a symptom of serious underlying medical illness.

If pregnant or breast-feeding

ask a health professional before use.

Keep out of the reach of children

In case of overdose, get medical help or contact a Poison Control Center right away.

Directions

adults & children 12 years of age and over: 1 gelcap (50 mg) at bedtime if needed, or as directed by a doctor

Other information

■ store at 20°-25°C (68°-77°F). See USP Controlled Temperature.

■ avoid high humidity

Inactive ingredients

ammonium hydroxide, black iron oxide, colloidal silicon dioxide, croscarmellose sodium, D&C red #33, dicalcium phosphate dihydrate, FD&C blue #1, FD&C yellow #6, gelatin, hydroxy propyl cellulose, hypromellose, isopropyl alcohol, lecithin, magnesium stearate, microcrystalline cellulose, n-butyl alcohol, polyethylene glycol, polyvinyl alcohol, propylene glycol, shellac, talc, titanium dioxide, xanthan gum.

Questions or comments?

call 1-877-770-3183 Mon-Fri 9:00 AM to 4:30 PM EST